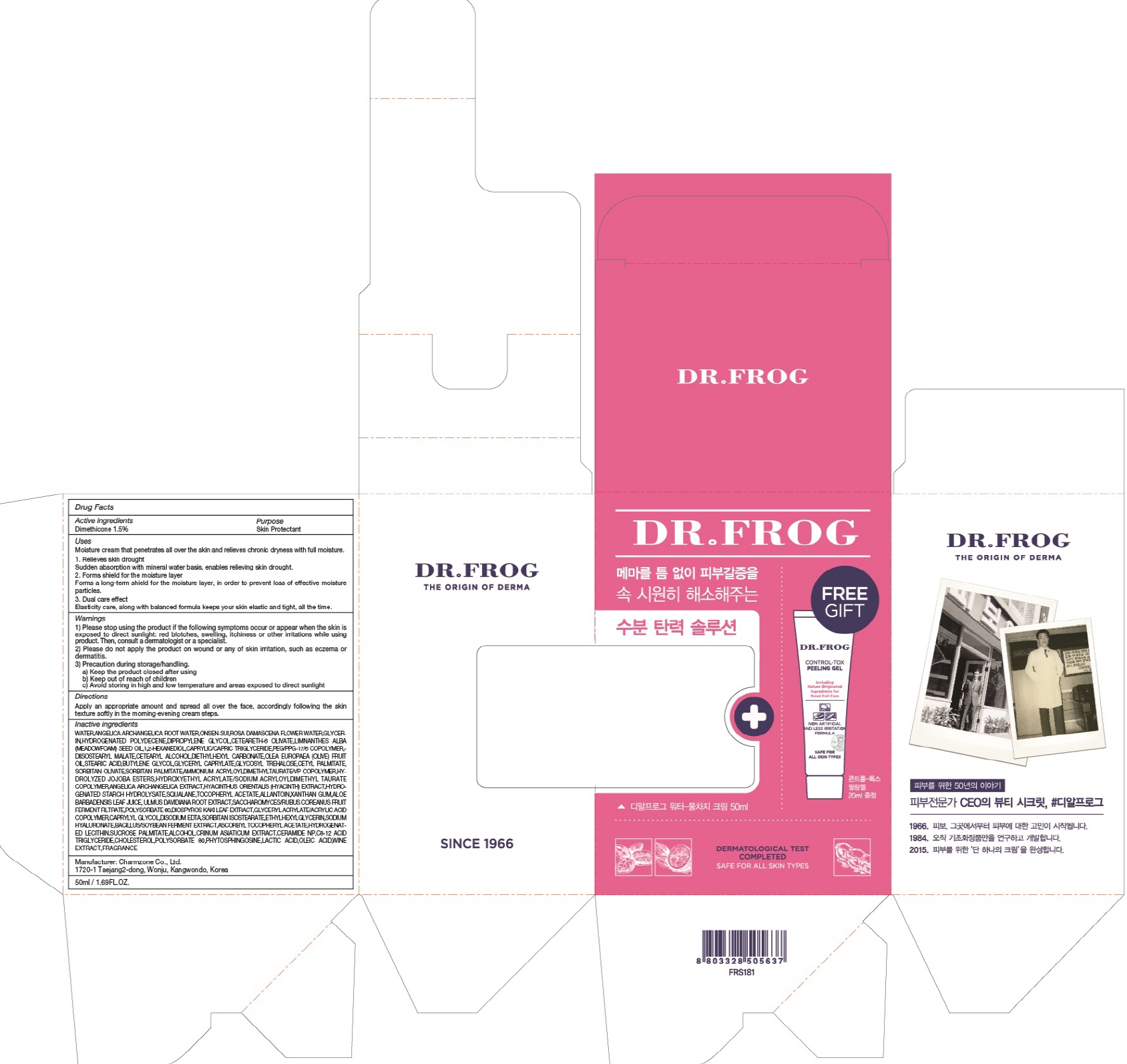 DRUG LABEL: DR FROG WATER FULL CHARGE
NDC: 22201-1010 | Form: CREAM
Manufacturer: Charmzone Co Ltd
Category: otc | Type: HUMAN OTC DRUG LABEL
Date: 20180413

ACTIVE INGREDIENTS: Dimethicone 0.75 g/50 mL
INACTIVE INGREDIENTS: WATER; GLYCERIN

ACTIVE INGREDIENT

Active ingredients: Dimethicone 1.5%

INACTIVE INGREDIENT

Inactive ingredients:

WATER,ANGELICA ARCHANGELICA ROOT WATER,ONSEN-SUI,ROSA DAMASCENA FLOWER WATER,GLYCERIN,HYDROGENATED POLYDECENE,DIPROPYLENE GLYCOL,CETEARETH-6 OLIVATE,LIMNANTHES ALBA (MEADOWFOAM) SEED OIL,1,2-HEXANEDIOL,CAPRYLIC/CAPRIC TRIGLYCERIDE,PEG/PPG-17/6 COPOLYMER,DIISOSTEARYL MALATE,CETEARYL ALCOHOL,DIETHYLHEXYL CARBONATE,OLEA EUROPAEA (OLIVE) FRUIT OIL,STEARIC ACID,BUTYLENE GLYCOL,GLYCERYL CAPRYLATE,GLYCOSYL TREHALOSE,CETYL PALMITATE,SORBITAN OLIVATE,SORBITAN PALMITATE,AMMONIUM ACRYLOYLDIMETHYLTAURATE/VP COPOLYMER,HYDROLYZED JOJOBA ESTERS,HYDROXYETHYL ACRYLATE/SODIUM ACRYLOYLDIMETHYL TAURATE COPOLYMER,ANGELICA ARCHANGELICA EXTRACT,HYACINTHUS ORIENTALIS (HYACINTH) EXTRACT,HYDROGENATED STARCH HYDROLYSATE,SQUALANE,TOCOPHERYL ACETATE,ALLANTOIN,XANTHAN GUM,ALOE BARBADENSIS LEAF JUICE, ULMUS DAVIDIANA ROOT EXTRACT,SACCHAROMYCES/RUBUS COREANUS FRUIT FERMENT FILTRATE,POLYSORBATE 60,DIOSPYROS KAKI LEAF EXTRACT,GLYCERYL ACRYLATE/ACRYLIC ACID COPOLYMER,CAPRYLYL GLYCOL,DISODIUM EDTA,SORBITAN ISOSTEARATE,ETHYLHEXYLGLYCERIN,SODIUM HYALURONATE,BACILLUS/SOYBEAN FERMENT EXTRACT,ASCORBYL TOCOPHERYL ACETATE,HYDROGENATED LECITHIN,SUCROSE PALMITATE,ALCOHOL,CRINUM ASIATICUM EXTRACT,CERAMIDE NP,C8-12 ACID TRIGLYCERIDE,CHOLESTEROL,POLYSORBATE 80,PHYTOSPHINGOSINE,LACTIC ACID,OLEIC ACID,WINE EXTRACT,FRAGRANCE

PURPOSE

Purpose: Skin Protectant

WARNINGS

1) Please stop using the product if the following symptoms occur or appear when the skin is exposed to direct sunlight: red blotches, swelling, itchiness or other irritations while using product. Then, consult a dermatologist or a specialist.

2) Please do not apply the product on wound or any of skin irritation, such as eczema or dermatitis.

3) Precaution during storage/handling. a) Keep the product closed after using b) Keep out of reach of children c) Avoid storing in high and low temperature and areas exposed to direct sunlight

KEEP OUT OF REACH OF CHILDREN

Uses

Moisture cream that penetrates all over the skin and relieves chronic dryness with full moisture.

1. Relieves skin drought Sudden absorption with mineral water basis, enables relieving skin drought

2. Forms shield for the moisture layer Forms a long-term shield for the moisture layer, in order to prevent loss of effective moisture particles. 3. Dual care effect Elasticity care, along with balanced formula keeps your skin elastic and tight, all the time.

Directions

Apply an appropriate amount and spread all over the face, accordingly following the skin texture softly in the morning∙evening cream steps.